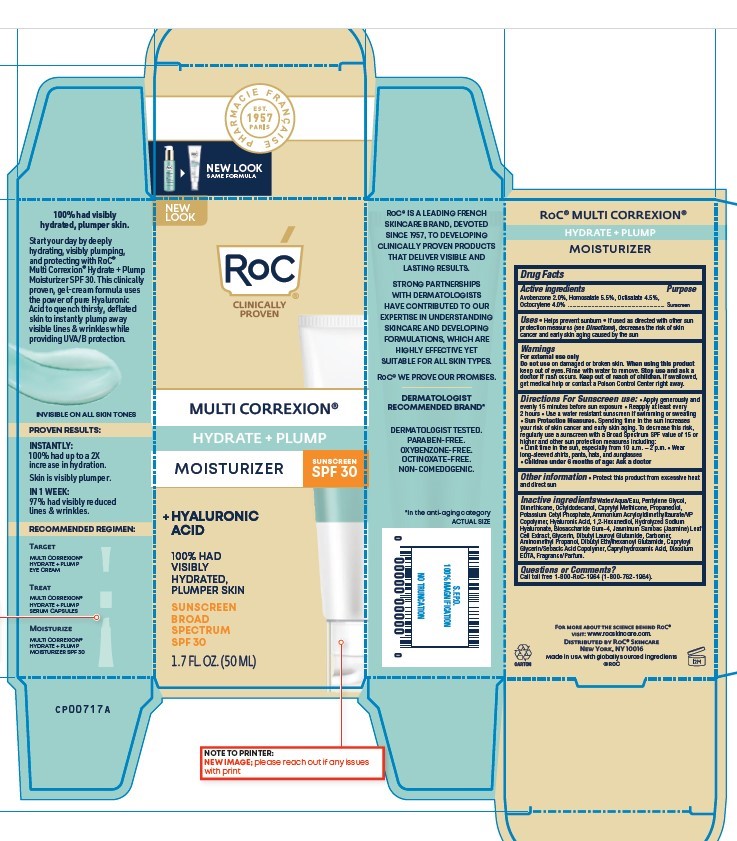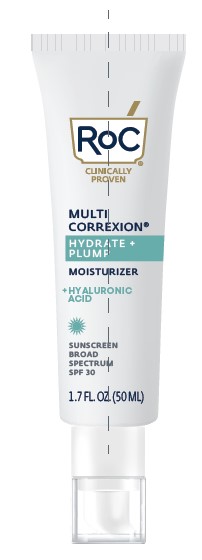 DRUG LABEL: ROC MULTI CORREXION HYDRATE AND PLUMP DAILY MOISTURISER SPF 30
NDC: 73496-005 | Form: LOTION
Manufacturer: Roc Skincare
Category: otc | Type: HUMAN OTC DRUG LABEL
Date: 20251210

ACTIVE INGREDIENTS: OCTISALATE 4.5 mg/100 mL; HOMOSALATE 5.5 mg/100 mL; AVOBENZONE 2 mg/100 mL; OCTOCRYLENE 4 mg/100 mL
INACTIVE INGREDIENTS: HYALURONATE SODIUM; AMINOMETHYLPROPANOL; CAPRYLYL TRISILOXANE; PENTYLENE GLYCOL; OCTYLDODECANOL; PROPANEDIOL; HYALURONIC ACID; AMMONIUM ACRYLOYLDIMETHYLTAURATE/VP COPOLYMER; DIBUTYL ETHYLHEXANOYL GLUTAMIDE; WATER; DIMETHICONE; POTASSIUM CETYL PHOSPHATE; BIOSACCHARIDE GUM-4; EDETATE DISODIUM; GLYCERIN; DIBUTYL LAUROYL GLUTAMIDE; CAPRYLHYDROXAMIC ACID; 1,2-HEXANEDIOL; CAPRYLOYL GLYCERIN/SEBACIC ACID COPOLYMER (2000 MPA.S); JASMINUM SAMBAC FLOWER; CARBOMER

MULTI CORREXION HYDRATE + PLUMP DAILY MOISTURISER SPF 30

Active Ingredients

Avobenzone 2.0%, Homosalate 5.5%, Octisalate 4.5%, Octocrylene 4.0%

Purpose

Sunscreen

Uses

- Helps prevent sunburn
- If used as directed with other sun protection measures (see Directions), decreases the risk of skin cancer and early skin aging caused by the sun

WARNINGS

For external use only

Do not use on damaged or broken skin.

When using this product keep out of eyes. Rinse with water to remove. Stop use and ask a doctor if rash occurs.

Keep out of reach of children. If swallowed, get medical help or contact a Poison Control Center right away.

Directions For Sunscreen Use:

- Apply generously and evenly 15 minutes before sun exposure
- Reapply at least every 2 hours
- Use a water resistant sunscreen if swimming or sweating
- Sun Protection Measures. Spending time in the sun increases your risk of skin cancer and early skin aging. To decrease this risk, regularly use a sunscreen with a Broad Spectrum SPF value of 15 or higher and other sun protection measures including:
- Limit time in the sun, especially from 10 a.m. - 2 p.m.
- Wear long-sleeved shirts, pants, hats, and sunglasses
- Children under 6 months of age: Ask a doctor

Other information

- Protect this product from excessive heat and direct sun

Inactive ingredients

Water/Aqua/Eau, Pentylene Glycol, Dimethicone, Octyldodecanol, Caprylyl Methicone, Propanediol, Potassium Cetyl Phosphate, Ammonium Acryloyldimethyltaurate/VP Copolymer, Hyaluronic Acid, 1,2-Hexanediol, Hydrolyzed Sodium Hyaluronate, Biosaccharide Gum-4, Jasminum Sambac (Jasmine) Leaf Cell Extract, Glycerin, Dibutyl Lauroyl Glutamide, Carbomer, Aminomethyl Propanol, Dibutyl Ethylhexanoyl Glutamide, Capryloyl Glycerin/Sebacic Acid Copolymer, Caprylhydroxamic Acid, Disodium EDTA, Fragrance/Parfum.

Questions or Comments?

Call toll free 1-800-RoC-1964 (1-800-762-1964)